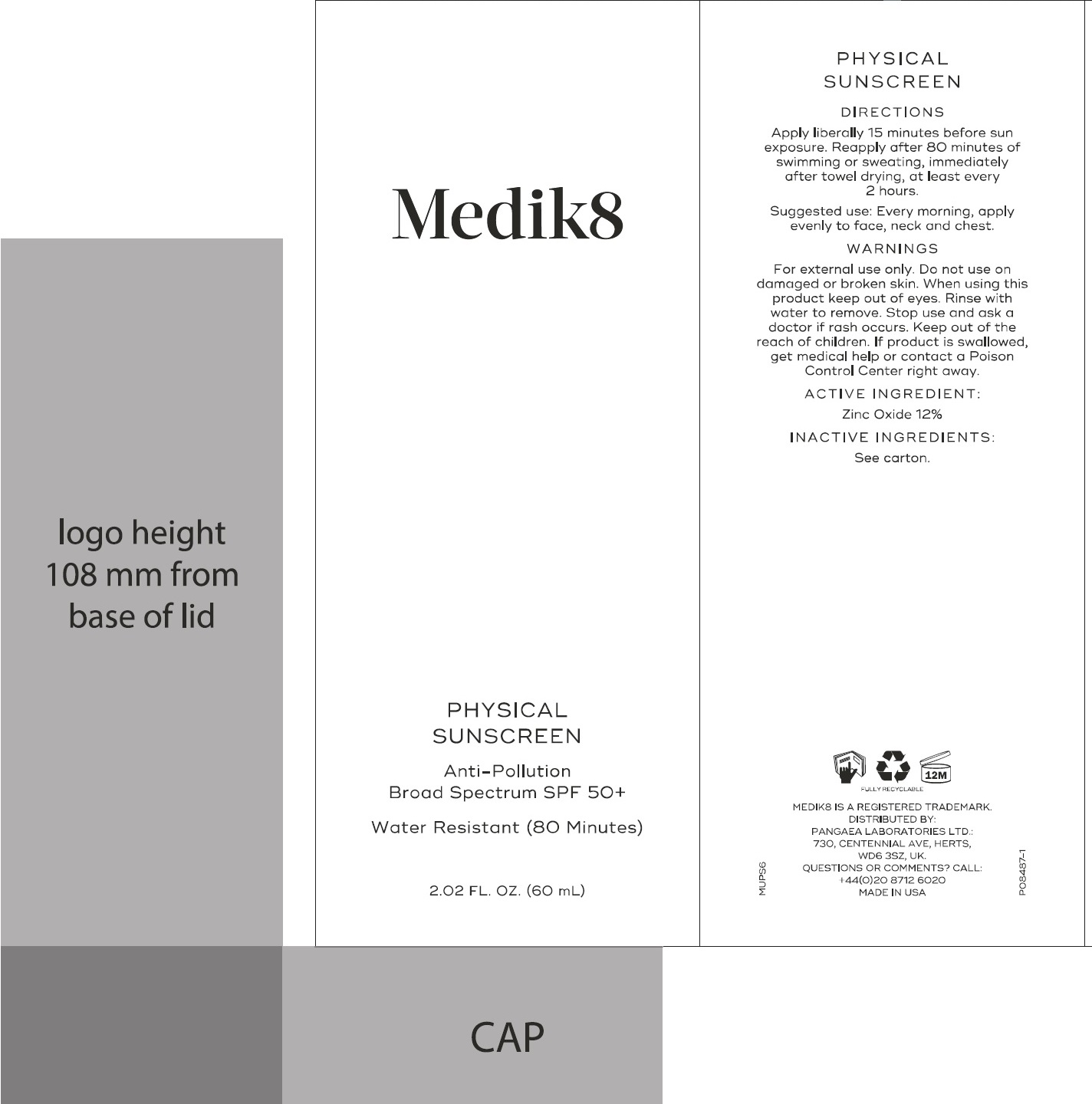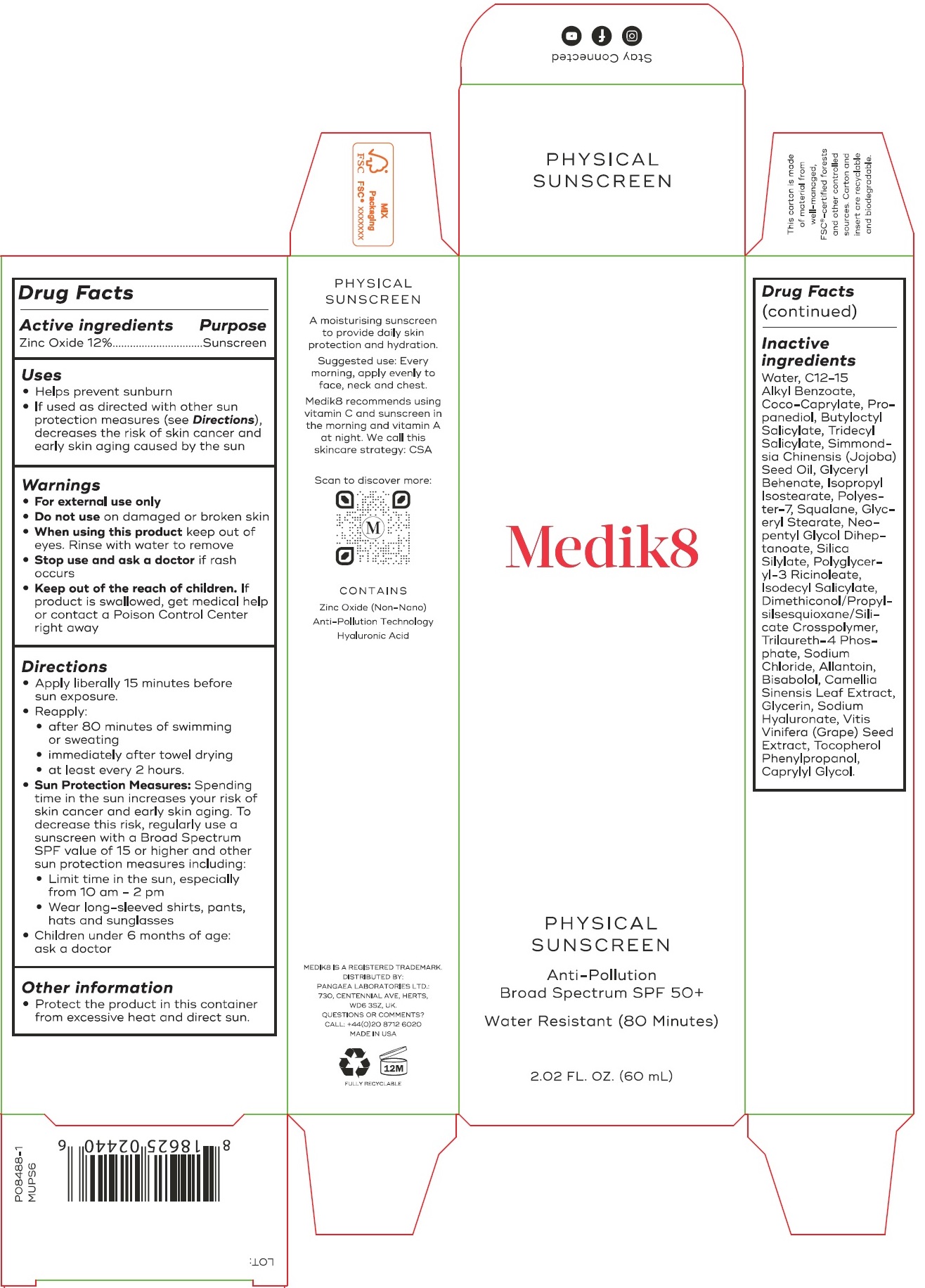 DRUG LABEL: Medik8 Physical Sunscreen SPF 50
NDC: 79988-001 | Form: CREAM
Manufacturer: Medik8 Limited
Category: otc | Type: HUMAN OTC DRUG LABEL
Date: 20240329

ACTIVE INGREDIENTS: ZINC OXIDE 120 mg/1 mL
INACTIVE INGREDIENTS: WATER; ALKYL (C12-15) BENZOATE; COCO-CAPRYLATE; PROPANEDIOL; BUTYLOCTYL SALICYLATE; JOJOBA OIL; ISOPROPYL ISOSTEARATE; POLYESTER-7; SQUALANE; GLYCERYL MONOSTEARATE; NEOPENTYL GLYCOL; POLYGLYCERYL-3 RICINOLEATE; ISODECYL SALICYLATE; TRILAURETH-4 PHOSPHATE; SODIUM CHLORIDE; ALLANTOIN; LEVOMENOL; GREEN TEA LEAF; GLYCERIN; HYALURONATE SODIUM; VITIS VINIFERA SEED; CAPRYLYL GLYCOL

Medik8 Physical Sunscreen SPF 50

Active ingredients

Zinc Oxide 12%

Purpose

Sunscreen

Uses

- Helps prevent sunburn
- If used as directed with other sun protection measures (see Directions), decreases the risk of skin cancer and early skin aging caused by the sun

Warnings

- For external use only

Do not use

- on damaged or broken skin

When using this product

- keep out of eyes. Rinse with water to remove

Stop use and ask a doctor

- if rash occurs

Keep out of reach of children.

If product is swallowed, get medical help or contact a Poison Control Center right away

Directions

- Apply liberally 15 minutes before sun exposure.
- Reapply:
- after 80 minutes of swimming or sweating
- immediately after towel drying
- at least every 2 hours.
- Sun Protections Measures. Spending time in the sun increases your risk of skin cancer and early skin aging. To decrease this risk, regurlarly use a sunscreen with a Broad Spectrum SPF value of 15 or higher and other sun protection measures including:
- Limit time in the sun, especially from 10 a.m. - 2 p.m.
- Wear long-sleeved shirts, pants, hats, and sunglasses
- Children under 6 months of age: ask a doctor

Other information

- Protect the product in this container from excessive heat and direct sun.

Inactive ingredients

Water, C12-15 Alkyl Benzoate, Coco-Caprylate, Propanediol, Butyloctyl Salicylate, Simmondsia Chinesis(Jojoba) Seed Oil, Glyceryl Behenate, Isopropyl Isostearate, Polyester-7, Squalane, Glyceryl Stearate, Neo-pentyl Glycol, Diheptanoate, Silica Silylate, Polyglyceryl-3 Ricinoleate, Isodecyl Salicylate, Dimethiconol/Propylsilesesquioxane/Silicate Crosspolymer, Trilaureth-4 Phosphate, Sodium Chloride, Allantoin, Bisabolol, Camellia Sinensis Leaf Extract, Glycerin, Sodium Hyaluronate, Vitis Vinifera (Grape) Seed Extract, Tocopherol Phenylpropanol, Caprylyl Glycol.